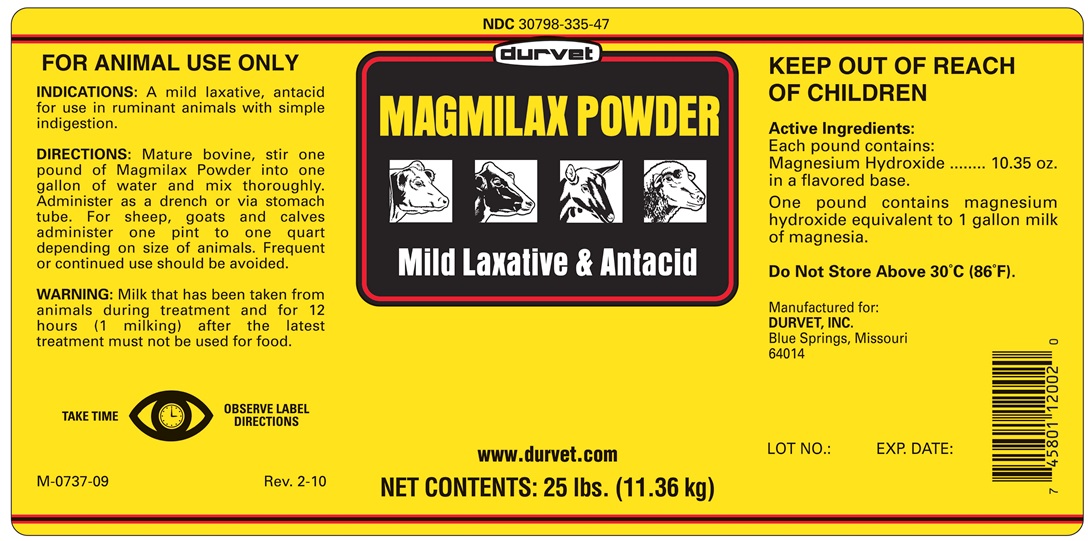 DRUG LABEL: Magmilax Powder
NDC: 30798-335 | Form: POWDER, FOR SOLUTION
Manufacturer: Durvet, Inc.
Category: animal | Type: OTC ANIMAL DRUG LABEL
Date: 20240603

ACTIVE INGREDIENTS: MAGNESIUM HYDROXIDE 454 g/454 g

MAGMILAX POWDER

INDICATIONS AND USAGE

MILD LAXATIVE AND ANTACID

FOR ANIMAL USE ONLY

KEEP OUT OF REACH OF CHILDREN

INDICATIONS

A mild laxative, antacid for use in ruminant animals with simple indigestion.

DIRECTIONS

Mature bovine, stir one pound of Magnalax Powder into one gallon of water and mix thoroughly.
Administer as a drench or via stomach tube. For sheep, goats and calves administer one pint to one quart
depending on size of animals. Frequent or continued use should be avoided.

WARNING

Milk that has been taken from animals during treatment and for 12 hours (1 milking)
after the latest treatment must not be used for food.

COMPONENTS

Each pound contains:

Active Ingredients:
Magnesium Hydroxide ...... 10.35 oz. in a flavored base.
One pound contains magnesium hydroxide equivalent to 1 gallon milk of magnesia.

STORAGE AND HANDLING

DO NOT STORE ABOVE 30o C (86oF)

TAKE TIME OBSERVE LABEL DIRECTIONS